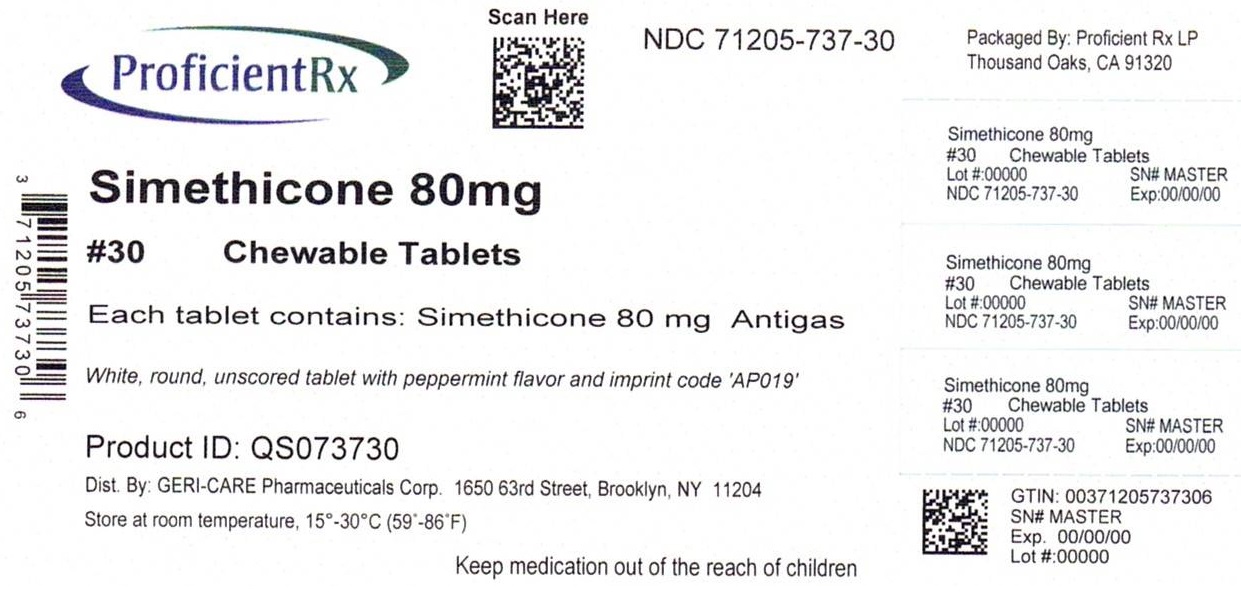 DRUG LABEL: GAS RELIEF
NDC: 71205-737 | Form: TABLET, CHEWABLE
Manufacturer: Proficient Rx LP
Category: otc | Type: HUMAN OTC DRUG LABEL
Date: 20240101

ACTIVE INGREDIENTS: DIMETHICONE 80 mg/1 1
INACTIVE INGREDIENTS: DEXTROSE, UNSPECIFIED FORM; SILICON DIOXIDE; SORBITOL; STEARIC ACID; MICROCRYSTALLINE CELLULOSE; MALTODEXTRIN; SUCROSE

gc 791a (799)

Active ingredient (in each tablet)

Simethicone 80 mg

Purpose

Anti-Gas

Uses

for the relief of

- pressure, bloating, and fullness commonly referred to as gas

Warnings

If pregnant or breast feeding, ask a health professional before use.

Keep out of reach of children. In case of overdose, get medical help or contact a Poison Control Center right away.

Directions

• chew thoroughly
• adults and children 12 years and over: take 1-2
tablets as needed after meals and at bedtime. Do
not exceed 6 tablets in 24 hours except under the
advice and supervision of a doctor.
• children under 12 years: ask a doctor

Other information

- Tamper Evident: Do not use if imprinted seal under cap is missing or broken
- store at room temperature, 15°C - 30°C (59˚F - 86˚F)

Inactive ingredients

dextrose, sugar, maltodextrin, microcrystalline cellulose, peppermint flavor, silica, sorbitol, stearic acid

Questions or comments?

1-800-540-3765